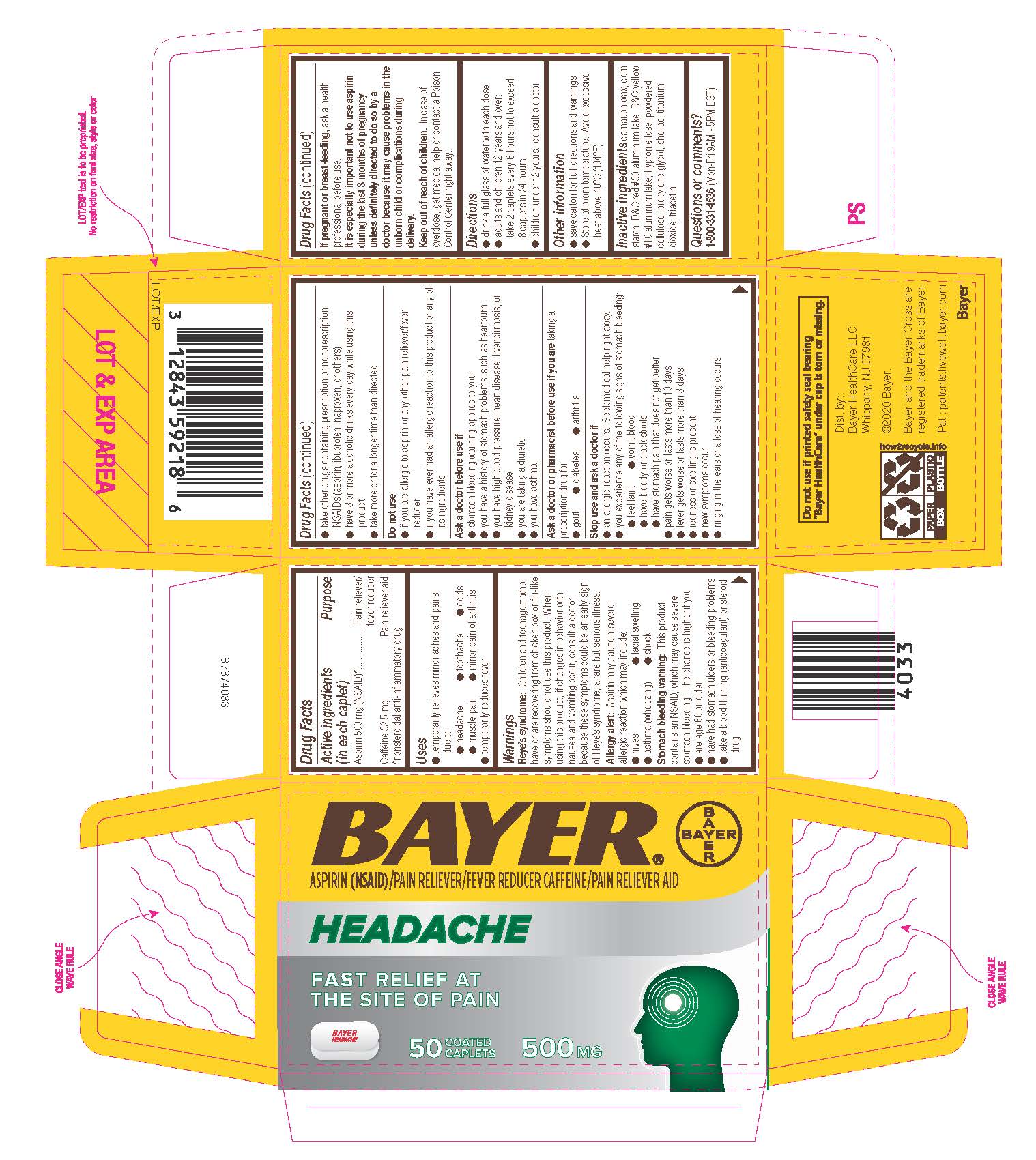 DRUG LABEL: Bayer Headache
NDC: 0280-0064 | Form: TABLET
Manufacturer: Bayer HealthCare LLC.
Category: otc | Type: HUMAN OTC DRUG LABEL
Date: 20251204

ACTIVE INGREDIENTS: ASPIRIN 500 mg/1 1; CAFFEINE 32.5 mg/1 1
INACTIVE INGREDIENTS: CARNAUBA WAX; HYPROMELLOSES; PROPYLENE GLYCOL; D&C YELLOW NO. 10 ALUMINUM LAKE; POWDERED CELLULOSE; TITANIUM DIOXIDE; STARCH, CORN; D&C RED NO. 30; TRIACETIN; SHELLAC

Bayer Headache UI 1600654

Drug Facts

Active ingredients (in each caplet) Purpose

Aspirin 500 mg (NSAID)*………………………...................Pain reliever/fever reducer

Caffeine 32.5 mg……………………………….....................Pain reliever aid

*nonsteroidal anti-inflammatory drug

Uses

- temporarily relieves minor aches and pains due to:
  - headache
  - toothache
  - colds
  - muscle pain
  - minor pain of arthritis
- temporarily reduces fever

Warnings

Reye’s syndrome: Children and teenagers who have or are recovering from chicken pox or flu-like symptoms should not use this product. When using this product, if changes in behavior with nausea and vomiting occur, consult a doctor because these symptoms could be an early sign of Reye’s syndrome, a rare but serious illness.

Allergy alert: Aspirin may cause a severe allergic reaction which may include: • hives • facial swelling • asthma (wheezing) • shock

Stomach bleeding warning: This product contains an NSAID, which may cause severe stomach bleeding. The chance is higher if you ● are age 60 or older ● have had stomach ulcers or bleeding problems ● take a blood thinning (anticoagulant) or steroid drug ● take other drugs containing prescription or nonprescription NSAIDs (aspirin, ibuprofen, naproxen, or others) ● have 3 or more alcoholic drinks every day while using this product ● take more or for a longer time than directed

Do not use

● if you are allergic to aspirin or any other pain reliever/fever reducer

● if you have ever had an allergic reaction to this product or any of its Ingredients

Ask a doctor before use if

● stomach bleeding warning applies to you

● you have a history of stomach problems, such as heartburn

● you have high blood pressure, heart disease, liver cirrhosis, or kidney disease

● you are taking a diuretic

● you have asthma

Ask a doctor or pharmacist before use if you are taking a prescription drug for

● gout

● diabetes

● arthritis

Stop use and ask a doctor if

- an allergic reaction occurs. Seek medical help right away.
- you experience any of the following signs of stomach bleeding:
  - feel faint
  - vomit blood
  - have bloody or black stools
  - have stomach pain that does not get better
- pain gets worse or lasts more than 10 days
- fever gets worse or lasts more than 3 days
- redness or swelling is present
- new symptoms occur
- ringing in the ears or a loss of hearing occurs

PREGNANCY OR BREAST FEEDING

If pregnant or breast-feeding, ask a health professional before use .

It is especially important not to use aspirin during the last 3 months of pregnancy unless definitely directed to do so by a doctor because it may cause problems in the unborn child or complications during delivery.

Keep out of reach of children. In case of overdose, get medical help or contact a Poison Control Center right away.

Directions

● drink a full glass of water with each dose

● adults and children 12 years and over: take 2 caplets every 6 hours not to exceed 8 caplets in 24 hours

● children under 12 years: consult a doctor

Other information

● save carton for full directions and warnings

● Store at room temperature. Avoid excessive heat above 40ºC (104ºF).

INACTIVE INGREDIENT

Inactive ingredients carnauba wax, corn starch, D&C red #30 aluminum lake, D&C yellow #10 aluminum lake, hypromellose, powdered cellulose, propylene glycol, shellac, titanium dioxide, triacetin

Questions or comments? 1-800-331-4536 (Mon-Fri 9AM - 5PM EST)

Package Display 50 Count Carton

Bayer®

ASPIRIN (NSAID)/PAIN RELIEVER/FEVER REDUCER CAFFEINE/PAIN RELIEVER AID

Headache

FAST RELIEF AT THE SITE OF PAIN

50 COATED CAPLETS

500 MG